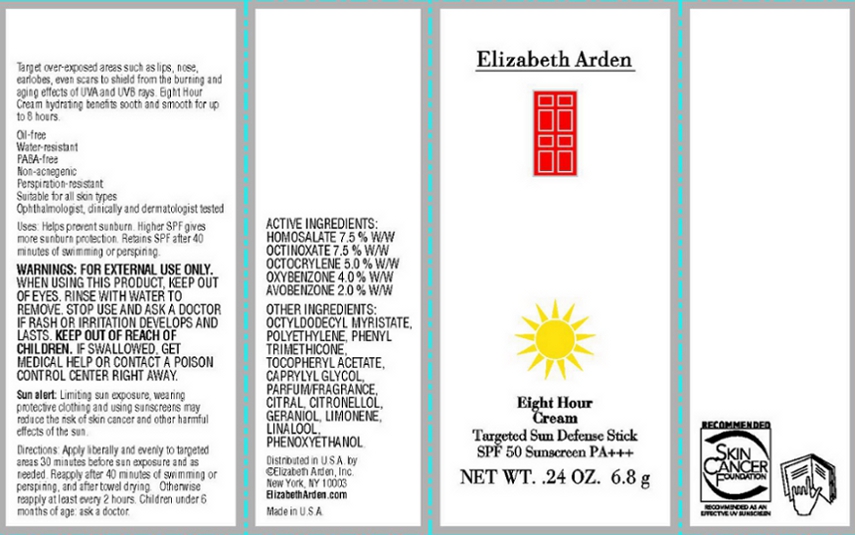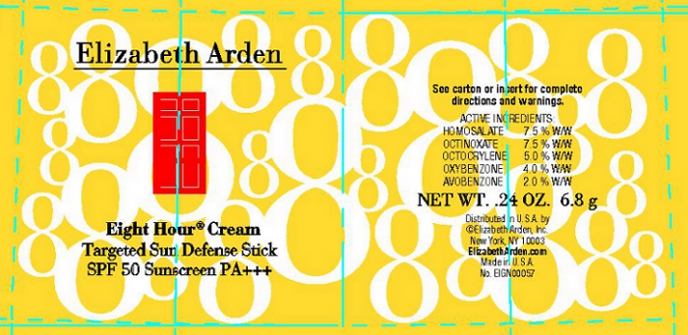 DRUG LABEL: Eight Hour Cream Targeted Sun Defense SPF 50
NDC: 67938-1130 | Form: STICK
Manufacturer: Elizabeth Arden, Inc
Category: otc | Type: HUMAN OTC DRUG LABEL
Date: 20110113

ACTIVE INGREDIENTS: HOMOSALATE 0.51 g/6.8 g; OCTINOXATE 0.51 g/6.8 g; OCTOCRYLENE 0.34 g/6.8 g; OXYBENZONE 0.27 g/6.8 g; AVOBENZONE 0.14 g/6.8 g
INACTIVE INGREDIENTS: OCTYLDODECYL MYRISTATE; PHENYL TRIMETHICONE; PHENOXYETHANOL; CAPRYLYL GLYCOL

BC1130

DESCRIPTION

Target over-exposed areas such as lips, nose, earlobes, even scars to shield from the burning and aging effects of UVA and UVB rays. Eight Hour Cream hydrating benefits sooth and smooth for up to 8 hours.

Oil-free. Water-resistant. PABA-free. Non-acnegenic. Perspiration-resistant. Suitable for all skin types. Ophthalmologist, clinically and dermatologist tested.

Uses: Helps prevent sunburn. Higher SPF gives more sunburn protection. Retains SPF after 40 minutes of swimming or perspiring.

Sun Alert: Limiting sun exposure, wearing protective clothing and using sunscreens may reduce the risk of skin cancer and other harmful effects of the sun.

INDICATIONS AND USAGE

Directions: Apply liberally and evenly to targeted areas 30 minutes before sun exposure and as needed. Reapply after 40 minutes of swimming or perspiring, and after towel drying. Otherwise, reapply at least every 2 hours. Children under 6 months of age: ask a doctor.

WARNINGS

Warnings: For external use only. When using this product, keep out of eyes. Rinse with water to remove. Stop use and ask a doctor if rash or irritation develops and lasts. Keep out of reach of children. If swallowed, get medical help or contact a poison controll center right away.

OTC - ACTIVE INGREDIENT

Active Ingredients: Homosalate 7.5% w/w, Octinoxate 7.5% w/w, Octocrylene 5.0% w/w, Oxybenzone 4.0% w/w, Avobenzone 2.0% w/w.

INACTIVE INGREDIENT

Other Ingredients: Octyldodecyl Myristate, Polyethylene, Phenyl Trimethicone, Tocopheryl Acetate, Caprylyl Glycol, Parfum/Fragrance, Citral, Citronellol, Geraniol, Limonene, Linalool, Phenoxyethanol.

DOSAGE & ADMINISTRATION

Apply evenly and liberally to targeted areas.

OTC - KEEP OUT OF REACH OF CHILDREN

Keep out of reach of children.

OTC - PURPOSE

Helps prevent sunburn. Higher SPF gives more sun protection.

OTC - WHEN USING

Keep out of eyes.